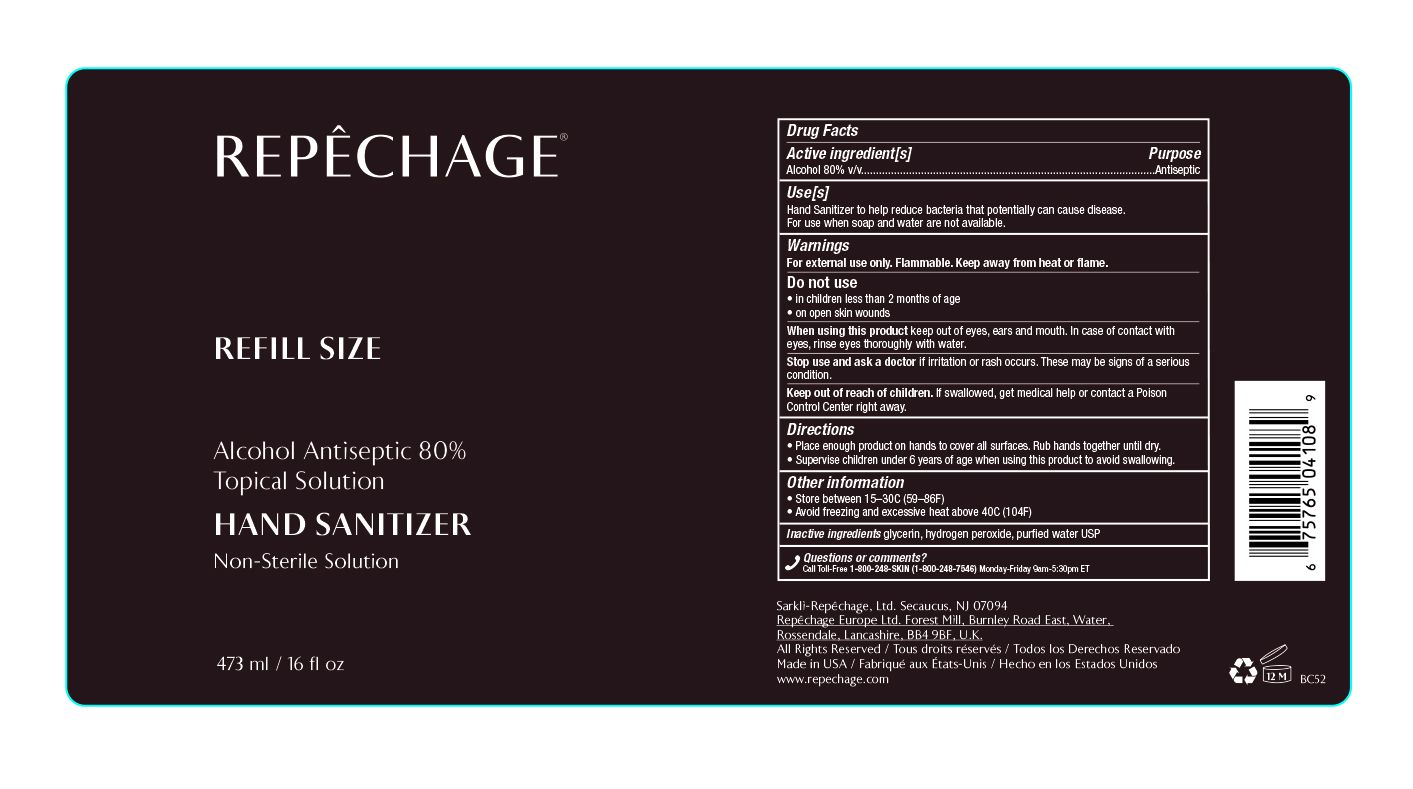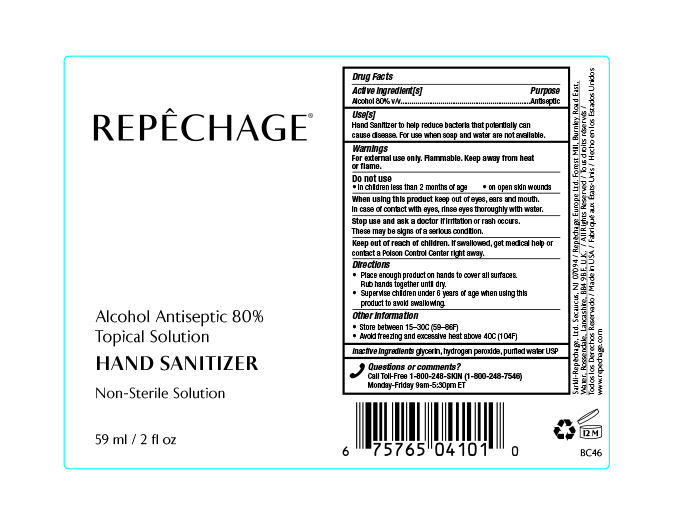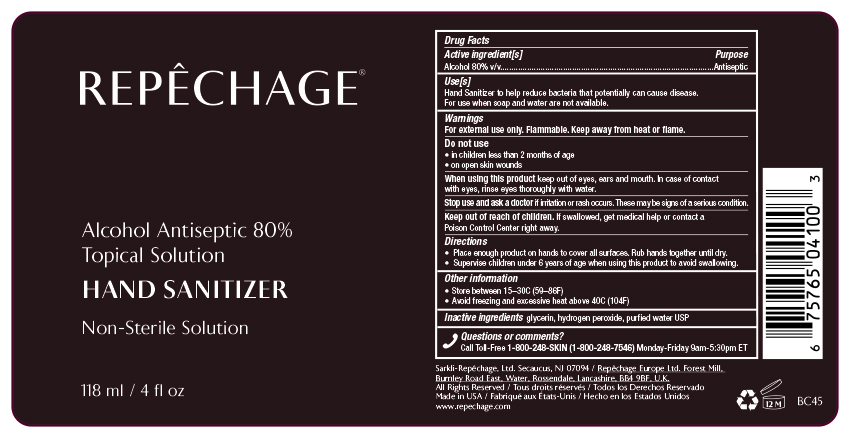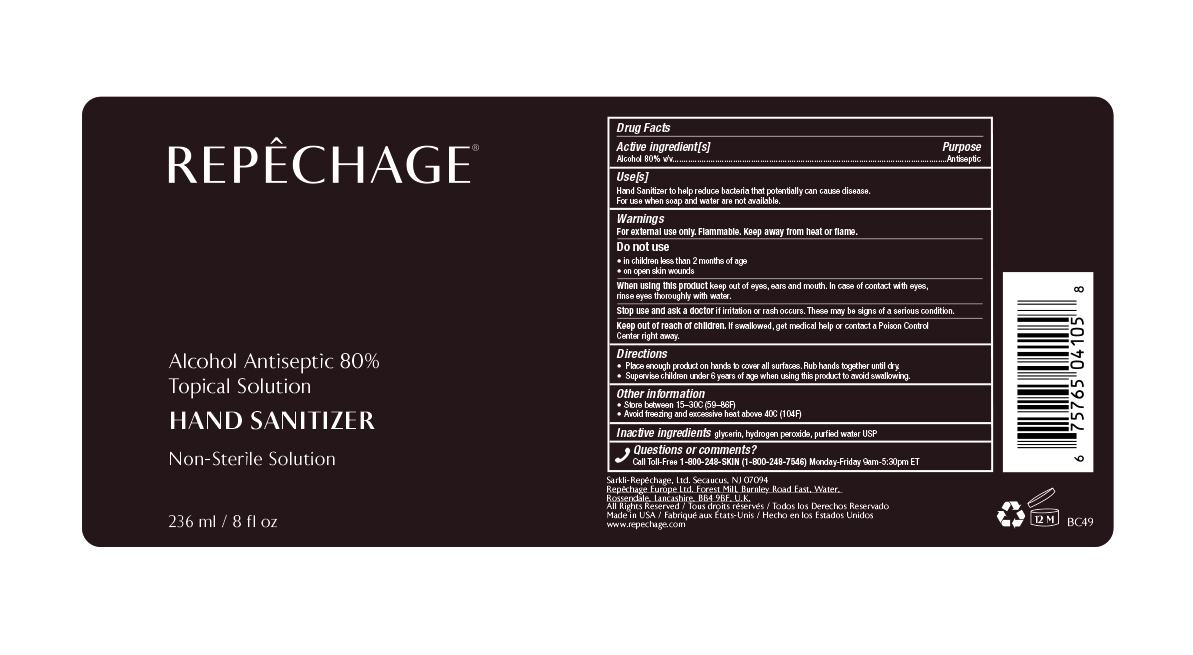 DRUG LABEL: Alcohol Antiseptic 80% Topical Solution Hand Sanitizer Non-Sterile Solution
NDC: 64521-5678 | Form: SOLUTION
Manufacturer: Sarkli-Repechage, Ltd.
Category: otc | Type: HUMAN OTC DRUG LABEL
Date: 20200414

ACTIVE INGREDIENTS: ALCOHOL 80 mL/100 mL
INACTIVE INGREDIENTS: GLYCERIN; WATER; HYDROGEN PEROXIDE

Repechage Alcohol Antiseptic 80% Topical Solution Hand Sanitizer Non-Sterile Solution

Active ingredient[s]
Alcohol 80% v/v

Purpose
Antiseptic

INDICATIONS AND USAGE

Use[s]
Hand Sanitizer to help reduce bacteria that potentially can cause disease.
For use when soap and water are not available.

Directions
• Place enough product on hands to cover all surfaces. Rub hands together until dry.
• Supervise children under 6 years of age when using this product to avoid swallowing.

Warnings
For external use only. Flammable. Keep away from heat or flame.

When using this product keep out of eyes, ears and mouth. In case of contact
with eyes, rinse eyes thoroughly with water.

STOP USE

Stop and ask a doctor if irritation or rash occurs. These may be signs of a serious
condition.

Keep out of reach of children. If swallowed, get medical help or contact a
Poison Control Center right away.

Directions
• Place enough product on hands to cover all surfaces. Rub hands together until dry.
• Supervise children under 6 years of age when using this product to avoid swallowing.

Directions
• Place enough product on hands to cover all surfaces. Rub hands together until dry.
• Supervise children under 6 years of age when using this product to avoid swallowing.

Other information
• Store between 15–30C (59–86F)
• Avoid freezing and excessive heat above 40C (104F)

Inactive ingredients glycerin, hydrogen peroxide, purfied water USP

Questions or comments?
Call Toll-Free 1-800-SKIN (1-800-248-7546) Monday-Friday 9am-5:30pm ET

Repechage Alcohol Antiseptic 80% Topical Solution Hand Sanitizer Non-Sterile Solution

118 mL, NDC 64521-5678-4

59 mL, NDC 64521-5678-2

236 mL, NDC 64521-5678-8

473 mL, NDC 64521-5678-1